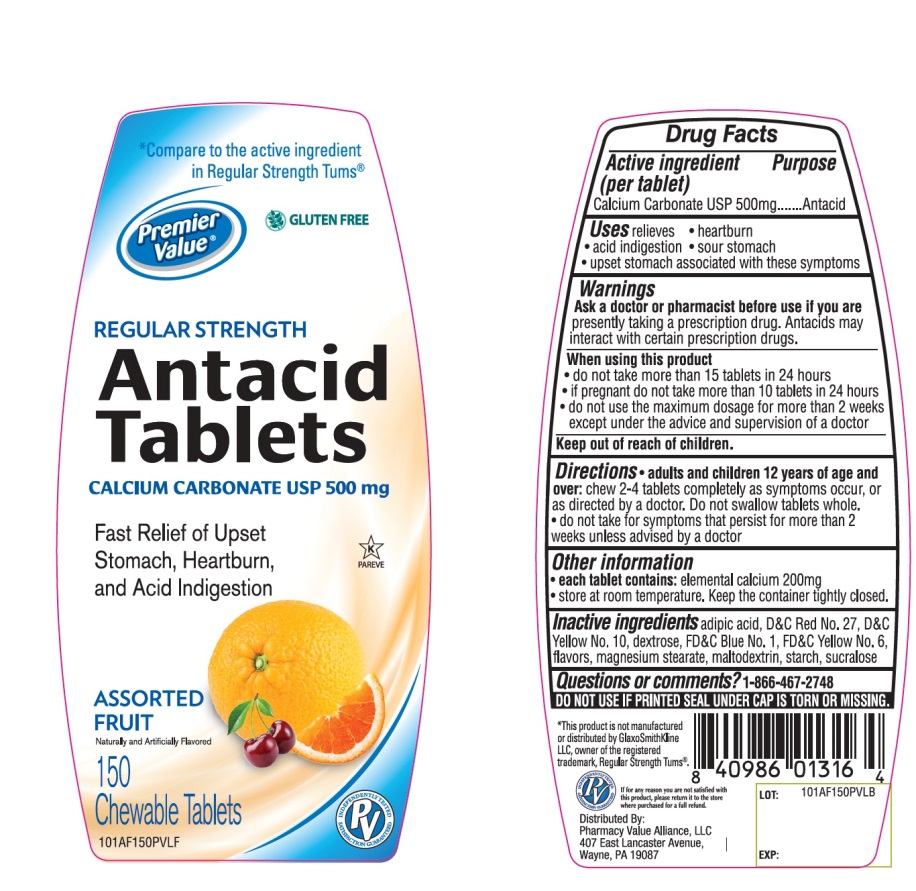 DRUG LABEL: Premier Value Chewable Antacid
NDC: 68016-652 | Form: TABLET, CHEWABLE
Manufacturer: Chain Drug Consortium, LLC
Category: otc | Type: HUMAN OTC DRUG LABEL
Date: 20241025

ACTIVE INGREDIENTS: CALCIUM CARBONATE 500 mg/1 1
INACTIVE INGREDIENTS: ADIPIC ACID; D&C RED NO. 27; D&C YELLOW NO. 10; DEXTROSE, UNSPECIFIED FORM; FD&C BLUE NO. 1; MAGNESIUM STEARATE; FD&C YELLOW NO. 6; MALTODEXTRIN; STARCH, CORN; SUCRALOSE

Premier Value Regular Strength Antacid Tablets

Active ingredient

Calcium Carbonate USP 500mg

Purpose

Antacid

Uses

relieves:

• heartburn

• sour stomach

• acid indigestion

• upset stomach associated with these symptoms

Warnings

Ask a doctor or pharmacist before use if you are taking a prescription drug. Antacids may interact with certain prescription drugs.

When using this product

• do not take more than 15 tablets in 24 hours

• do not use the maximum dosage for more than 2 weeks except under the advice and supervision of a doctor

Directions

• adults and children 12 years of age and over: chew 2-4 tablets as symptoms occur, or as directed by a doctor. Do not swallow tablets whole.

• do not take for symptoms that persist for more than 2 weeks unless advised by a doctor

Other Information

• each tablets contains: elemental calcium 200mg

• store at room temperature. Keep the container tightly closed

Inactive ingredients

adipic acid, D&C Red No. 27, D&C Yellow No. 10, dextrose, FD&C Blue No. 1, FD&C Yellow No. 6, flavor, magnesium stearate, maltodextrin, starch, sucralose

Package/Label Principal Display Panel

*Compare to the active ingredient in Regular Strength Tums®

Premier Value®

REGULAR STRENGTH

Antacid Tablets

CALCIUM CARBONATE USP 500mg

For Fast Relief of Heartburn, Acid Indigestion & Upset Stomach

ASSORTED FRUIT

Naturally and Artificially Flavored

150 Chewable Tablets

Distributed by

Pharmacy Value Alliance, LLC

407 East Lancaster Avenue,

Wayne, PA 19087

*This product is not manufactured or distributed by GlaxoSmithKline LLC, owner of the registered trademark, Regular Strength of Tums®

Premier Value Regular Strength Assorted Fruit Antacid Tablets